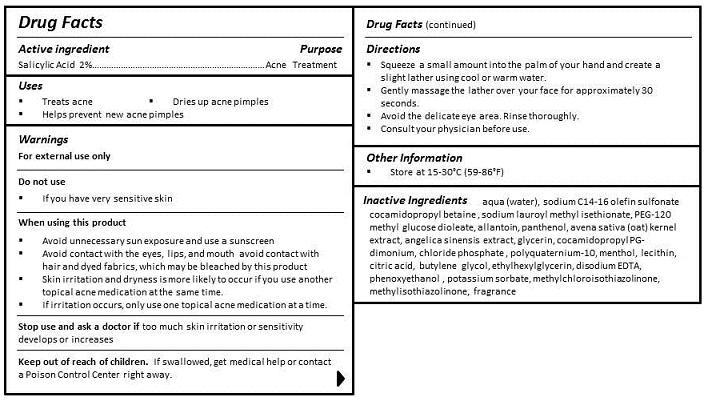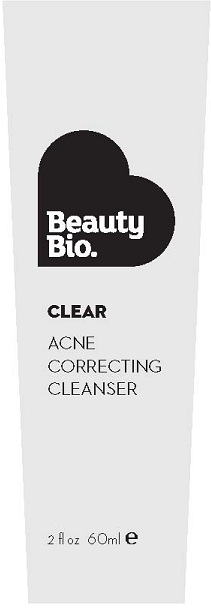 DRUG LABEL: ACNE CORRECTING CLEANSER
NDC: 54272-101 | Form: GEL
Manufacturer: CEN BEAUTY LLC
Category: otc | Type: HUMAN OTC DRUG LABEL
Date: 20130223

ACTIVE INGREDIENTS: SALICYLIC ACID 2 g/100 mL
INACTIVE INGREDIENTS: WATER; SODIUM C14-16 OLEFIN SULFONATE; COCAMIDOPROPYL BETAINE; SODIUM LAUROYL 1-METHYL ISETHIONATE; PEG-120 METHYL GLUCOSE DIOLEATE; ALLANTOIN; PANTHENOL; OAT; ANGELICA SINENSIS WHOLE; GLYCERIN; COCAMIDOPROPYL PG-DIMONIUM CHLORIDE PHOSPHATE; POLYQUATERNIUM-10 (400 CPS AT 2%); MENTHOL; LECITHIN, SOYBEAN; ANHYDROUS CITRIC ACID; BUTYLENE GLYCOL; ETHYLHEXYLGLYCERIN; EDETATE DISODIUM; PHENOXYETHANOL; POTASSIUM SORBATE; METHYLCHLOROISOTHIAZOLINONE; METHYLISOTHIAZOLINONE

ACTIVE INGREDIENT

SALICYLIC ACID 2%

PURPOSE

ACNE TREATMENT

USES

- TREATS ACNE
- DRIES UP ACNE PIMPLES
- HELPS PREVENT NEW ACNE PIMPLES

WARNINGS

FOR EXTERNAL USE ONLY

DO NOT USE

- IF YOU HAVE VERY SENSITIVE SKIN

STOP USE AND ASK A DOCTOR IF TOO MUCH SKIN RRITATION OR SENSITIVITY DEVELOPS OR INCREASES.

KEEP OUT OF REACH OF CHILDREN. IF SWALLOWED, GET MEDICAL HELP OR CONTACT A POISON CONTROL CENTER RIGHT AWAY.

DIRECTIONS

- Squeeze a small amount into the palm of your hand and create a slight lather using cool or warm water.
- Gently massage the lather over your face for approximately 30 seconds.
- Avoid the delicate eye area. Rinse thoroughly.
- Consult your physician before use.

Other Information

Store at 15-30°C (59-86°F)

INACTIVE INGREDIENT

INGREDIENTS

aqua (water), sodium C14-16 olefin sulfonate cocamidopropyl betaine , sodium lauroyl methyl isethionate, PEG-120 distearate, allantoin, panthenol, avena sativa (oat) kernel extract, angelica sinensis extract, glycerin, cocamidopropyl PG-dimonium, chloride phosphate, polyquaternium-10, menthol, lecithin, citric acid, butylene glycol, ethylhexylglycerin, disodium EDTA, phenoxyethanol, potassium sorbate, methylchloroisothiazolinone, methylisothiazolinone, fragrance